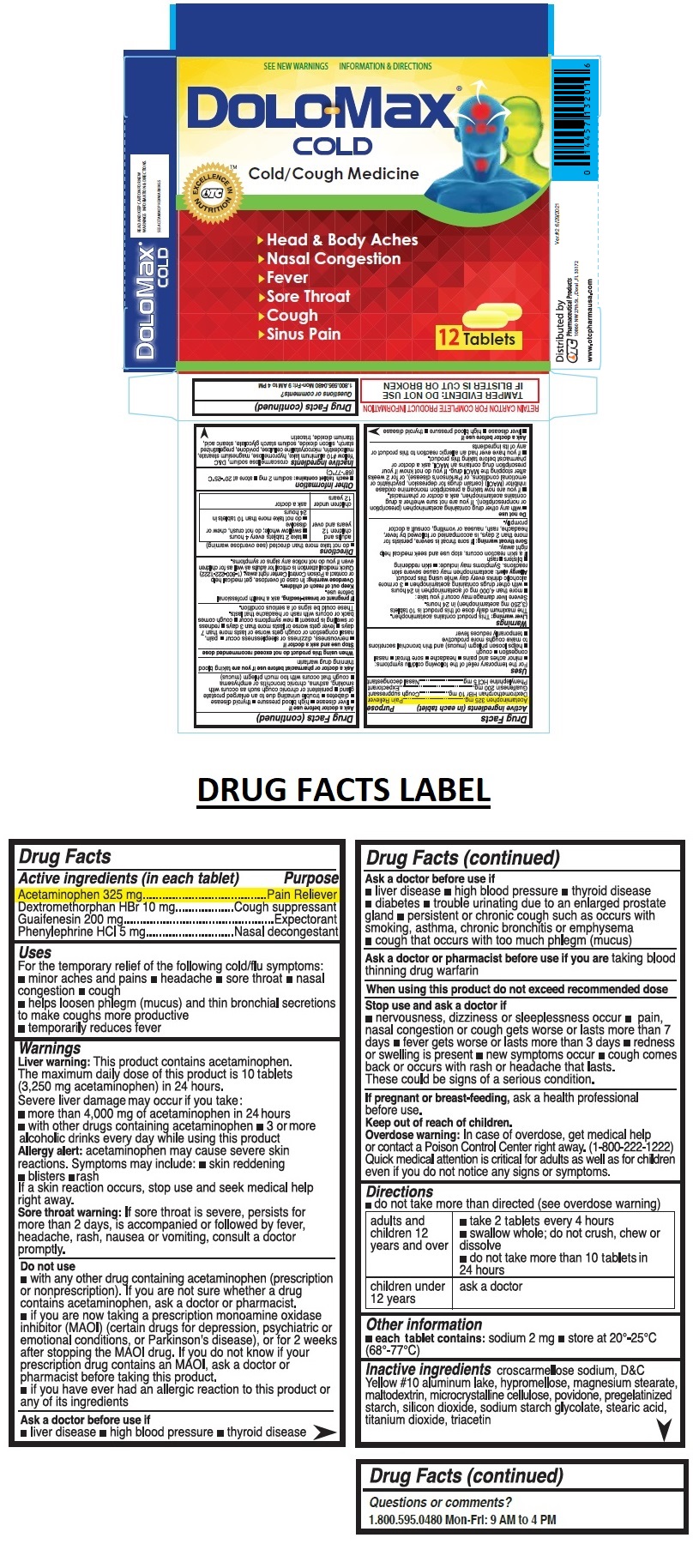 DRUG LABEL: DoloMax Cold Cough
NDC: 55959-133 | Form: TABLET
Manufacturer: BENARD INDUSTRIES INC
Category: otc | Type: HUMAN OTC DRUG LABEL
Date: 20241031

ACTIVE INGREDIENTS: ACETAMINOPHEN 325 mg/1 1; DEXTROMETHORPHAN HYDROBROMIDE 10 mg/1 1; GUAIFENESIN 200 mg/1 1; PHENYLEPHRINE HYDROCHLORIDE 5 mg/1 1
INACTIVE INGREDIENTS: CROSCARMELLOSE SODIUM; D&C YELLOW NO. 10 ALUMINUM LAKE; HYPROMELLOSE, UNSPECIFIED; MAGNESIUM STEARATE; MALTODEXTRIN; MICROCRYSTALLINE CELLULOSE; POVIDONE, UNSPECIFIED; STARCH, CORN; SILICON DIOXIDE; SODIUM STARCH GLYCOLATE TYPE A; STEARIC ACID; TITANIUM DIOXIDE; TRIACETIN

DoloMax® Cold Cough

Active ingredients (in each tablet)

Acetaminophen 325 mg
Dextromethorphan HBr 10 mg
Guaifenesin 200 mg
Phenylephrine HCl 5 mg

Purpose

Pain Reliever
Cough suppressant
Expectorant
Nasal decongestant

Uses

For the temporary relief of the following cold/flu symptoms:
• minor aches and pains • headache • sore throat • nasal congestion • cough
• helps loosen phlegm (mucus) and thin bronchial secretions to make coughs more productive
• temporarily reduces fever

Warnings

Liver warning: This product contains acetaminophen.
The maximum daily dose of this product is 10 tablets (3,250 mg acetaminophen) in 24 hours.
Severe liver damage may occur if you take :
• more than 4,000 mg of acetaminophen in 24 hours • with other drugs containing acetaminophen • 3 or more alcoholic drinks every day while using this product
Allergy alert: acetaminophen may cause severe skin reactions. Symptoms may include: • skin reddening • blisters • rash
If a skin reaction occurs, stop use and seek medical help right away.
Sore throat warning: If sore throat is severe, persists for more than 2 days, is accompanied or followed by fever, headache, rash, nausea, or vomiting, consult a doctor promptly.

Do not use
• with any other drug containing acetaminophen (prescription or nonprescription). If you are not sure whether a drug contains acetaminophen, ask a doctor or pharmacist.
• if you are now taking a prescription monoamine oxidase inhibitor (MAOI) (certain drugs for depression, psychiatric or emotional conditions, or Parkinson's disease), or for 2 weeks after stopping the MAOI drug. If you do not know if your prescription drug contains an MAOI, ask a doctor or pharmacist before taking this product.
• if you have ever had an allergic reaction to this product or any of its ingredients

Ask a doctor before use if
• liver disease • high blood pressure • thyroid disease • diabetes • trouble urinating due to an enlarged prostate gland • persistent or chronic cough such as occurs with smoking, asthma, chronic bronchitis or emphysema • cough that occurs with too much phlegm (mucus)

Ask a doctor or pharmacist before use if you are taking blood thinning drug warfarin

When using this product do not exceed recommended dose

Stop use and ask a doctor if
• nervousness, dizziness, or sleeplessness occur • pain, nasal congestion or cough gets worse or lasts more than 7 days • fever gets worse or lasts more than 3 days • redness or swelling is present • new symptoms occur • cough comes back or occurs with rash or headache that lasts.
These could be signs of a serious condition.

If pregnant or breast-feeding, ask a health professional before use.

Keep out of reach of children.
Overdose warning: In case of overdose, get medical help or contact a Poison Control Center right away. (1-800-222-1222)
Quick medical attention is critical for adults as well as for children even if you do not notice any signs or symptoms.

Directions

• do not take more than directed (see overdose warning)

adults and children 12 years and over | • take 2 tablets every 4 hours • swallow whole; do not crush, chew or dissolve • do not take more than 10 tablets in 24 hours
children under 12 years | ask a doctor

Other information

• each tablet contains: sodium 2 mg • store at 20°-25°C (68°-77°C)

Inactive ingredients

croscarmellose sodium, D&C Yellow #10 aluminum lake, hypromellose, magnesium stearate, maltodextrin, microcrystalline cellulose, povidone, pregelatinized starch, silicon dioxide, sodium starch glycolate, stearic acid, titanium dioxide, triacetin

Questions or comments?

1.800.595.0480 Mon-Fri: 9 AM to 4 PM

SEE NEW WARNINGS INFORMATION & DIRECTIONS

Cold/Cough Medicine

OTC EXCELLENCE IN NUTRITIONTM

› Head & Body Aches
› Nasal Congestion
› Fever
› Sore Throat
› Cough
› Sinus Pain

READ AND KEEP CARTON FOR NEW WARNINGS INFORMATION & DIRECTIONS.

SEE ACETAMINOPHEN WARNINGS

RETAIN CARTON FOR COMPLETE PRODUCT INFORMATION

TAMPER EVIDENT: DO NOT USE IF BLISTER IS CUT OR BROKEN

Distributed by
OTC Pharmaceutical Products
10860 Nw 27th St , Doral , FL 33172

www.otcpharmausa.com